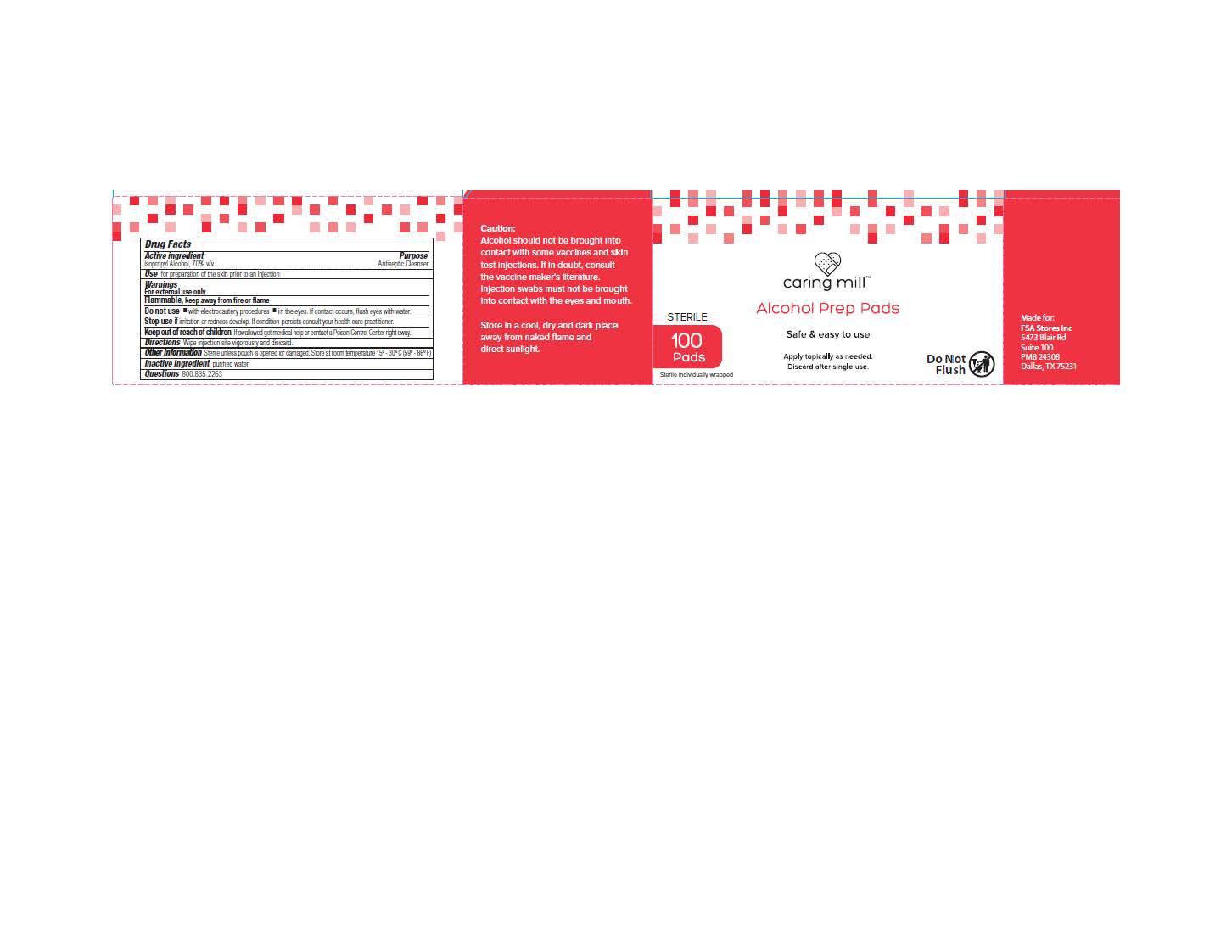 DRUG LABEL: Caring Mill Alcohol Prep Pads
NDC: 81522-505 | Form: SWAB
Manufacturer: FSA Store Inc.
Category: otc | Type: HUMAN OTC DRUG LABEL
Date: 20250731

ACTIVE INGREDIENTS: ISOPROPYL ALCOHOL 0.7 mL/1 mL
INACTIVE INGREDIENTS: WATER

Caring Mill Alcohol Prep Pads

Drug Facts

Active Ingredient

Isopropyl Alcohol, 70% v/v

Purpose

Antiseptic Cleanser

INDICATIONS AND USAGE

Use • for preparation of the skin prior to an injection

WARNINGS

Warnings● For external use only ● Flammable, keep away from fire or flame

Do Not Use ● with electrocautery procedures ● In the eyes. If contact occurs, flush

eyes with water

STOP USE

Slop Use If irritation and redness develop. If condition persists consult your health care practitioner.

Keep out of reach of children. If swallowed, get medical help or consult a Poison

Control Center right away.

DOSAGE AND ADMINISTRATION

Directions Wipe injection site vigorously and discard

Other Information Sterile unless pouch is opened or damaged.Store at room temperature 15ο - 30ο C (59ο - 86ο F)

Inactive Ingredient purified water

Questions

800 835 2263

PACKAGE LABEL

Carton Image